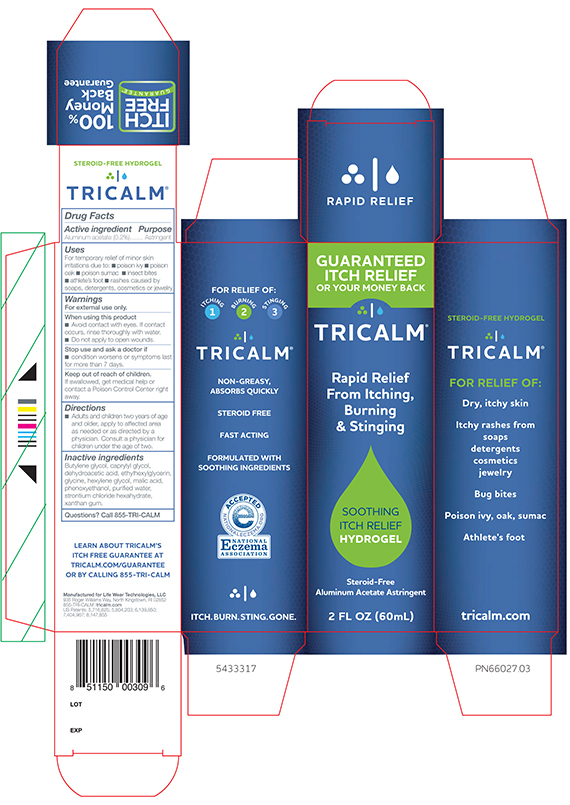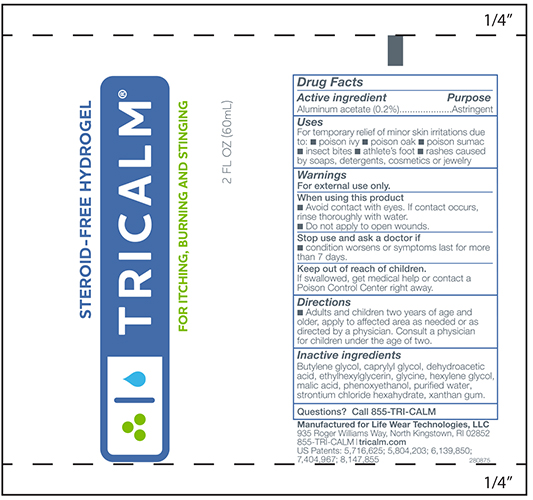 DRUG LABEL: TriCalm 
NDC: 71207-100 | Form: GEL
Manufacturer: Modular Thermal Technologies LLC Dba Life Wear Technologies 
Category: otc | Type: HUMAN OTC DRUG LABEL
Date: 20170323

ACTIVE INGREDIENTS: ALUMINUM ACETATE 2 mg/1 mL
INACTIVE INGREDIENTS: BUTYLENE GLYCOL; CAPRYLYL GLYCOL; DEHYDROACETIC ACID; ETHYLHEXYLGLYCERIN; GLYCINE; HEXYLENE GLYCOL; MALIC ACID; PHENOXYETHANOL; WATER; STRONTIUM CHLORIDE HEXAHYDRATE; XANTHAN GUM

TriCalm®
Hydrogel

Drug Facts

Active ingredient

Aluminum acetate (0.2%)

Purpose

Astringent

Uses

For temporary relief of minor skin irritations due to:

- poison ivy
- poison oak
- poison sumac
- insect bites
- athlete's foot
- rashes caused by soaps, detergents, cosmetics or jewelry

Warnings

For external use only.

When using this product

- Avoid contact with eyes. If contact occurs, rinse thoroughly with water.
- Do not apply to open wounds.

Stop use and ask a doctor if

- condition worsens or symptoms last for more than 7 days.

Keep out of reach of children.

- If swallowed, get medical help or contact a Poison Control Center right away.

Directions

- Adults and children two years of age and older, apply to affected area as needed or as directed by a physician.
- Consult a physician for children under the age of two.

Inactive ingredients

Butylene glycol, caprylyl glycol, dehydroacetic acid, ethylhexylglycerin, glycine, hexylene glycol, malic acid, phenoxyethanol, purified water, strontium chloride hexahydrate, xanthan gum.

Questions?

Call 855-TRI-CALM

PRINCIPAL DISPLAY PANEL - 60 mL Vertical Carton

TRICALM®

Rapid Relief
From Itching,
Burning
& Stinging

SOOTHING
ITCH RELIEF
HYDROGEL

Steroid-Free
Aluminum Acetate Astringent

2 FL OZ (60mL)

Principal Display Panel Tube

TRICALM Steroid-Free Hydrogel

For Itching Burning and Stinging

2.0 FLOZ (60mL)